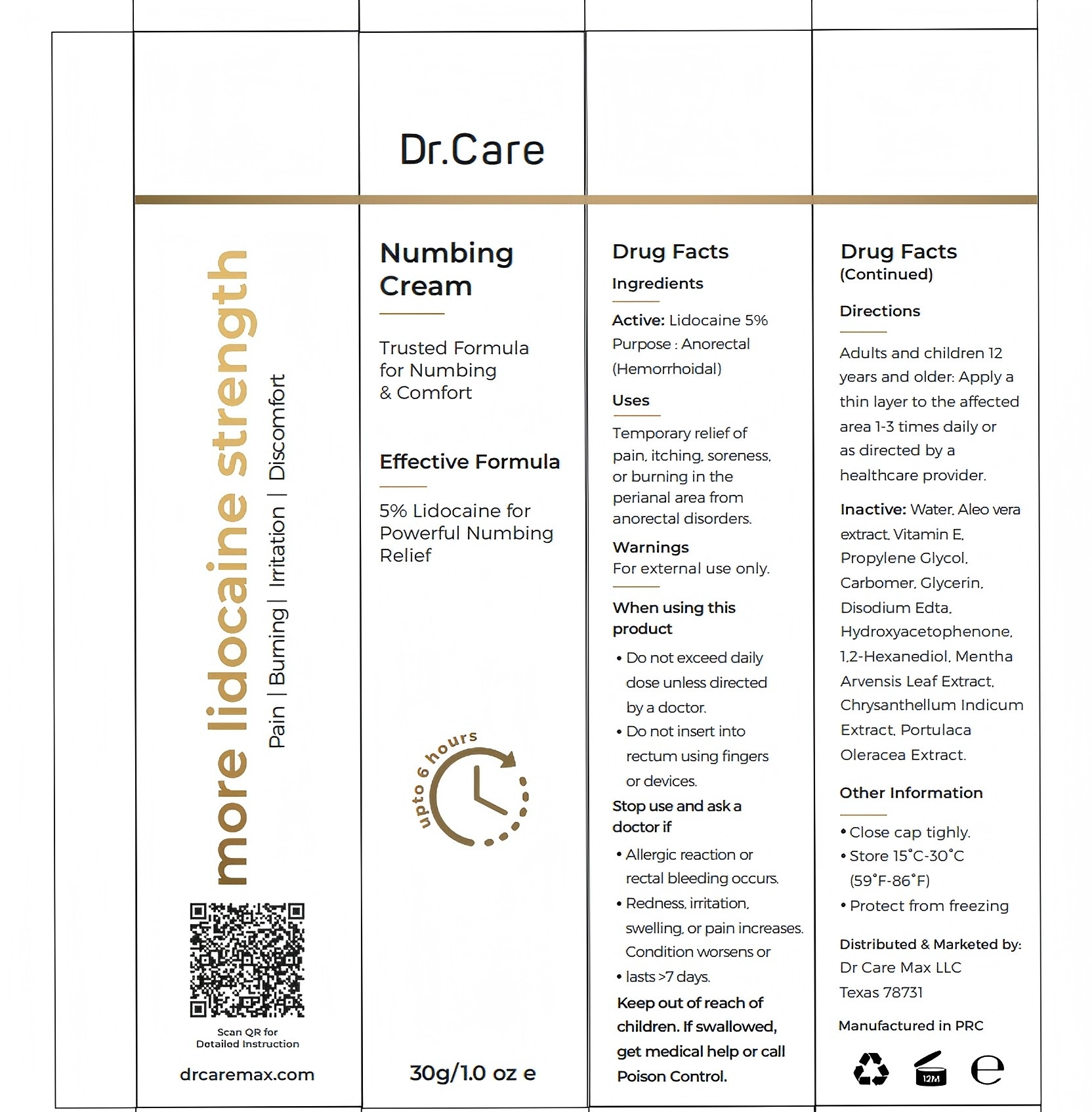 DRUG LABEL: Dr. Care Numbing Cream
NDC: 84019-038 | Form: CREAM
Manufacturer: Shengnan (Guangzhou) Cosmetics Co., LTD
Category: otc | Type: HUMAN OTC DRUG LABEL
Date: 20260107

ACTIVE INGREDIENTS: LIDOCAINE 50 mg/1 g
INACTIVE INGREDIENTS: CARBOMER; 1,2-HEXANEDIOL; HYDROXYACETOPHENONE; WATER; GLYCERIN

Dr. Care Numbing Cream 30g/1.0 oz e

WARNINGS

For external use only.

PURPOSE

Anorectal
(Hemorrhoidal)

STOP USE

Allergic reaction or
rectal bleeding occurs.
Redness, irritation,
swelling, or pain increases.
Condition worsens or
lasts >7 days

ACTIVE INGREDIENT

5% Lidocaine

WHEN USING

Do not exceed daily
dose unless directed
by a doctor.
Do not insert into
rectum using fingers
or devices.

INACTIVE INGREDIENT

Water, Aleo vera
extract, Vitamin E,
Propylene Glycol,
Carbomer, Glycerin,
Disodium Edta,
Hydroxyacetophenone,
1,2-Hexanediol, Mentha
Arvensis Leaf Extract,
Chrysanthellum Indicum
Extract, Portulaca
Oleracea Extract.

DOSAGE AND ADMINISTRATION

Adults and children 12
years and older: Apply a
thin layer to the affected
area 1-3 times daily or
as directed by a
healthcare provider.

INDICATIONS AND USAGE

Temporary relief of
pain, itching, soreness,
or burning in the
perianal area from
anorectal disorders.

Keep out of reach of
children. If swallowed,
get medical help or call
Poison Control.